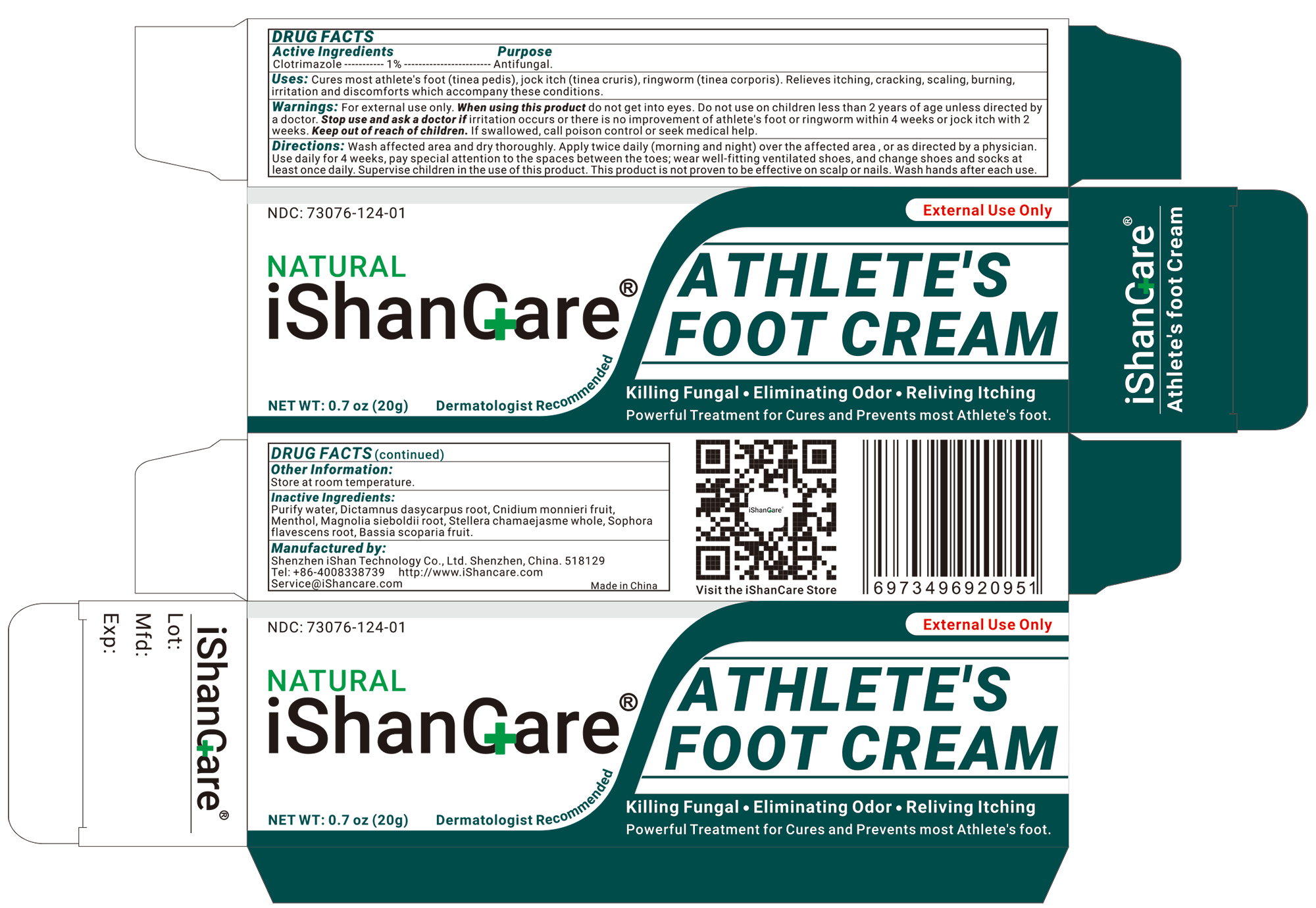 DRUG LABEL: iShancare Athletes Foot Cream
NDC: 73076-150 | Form: CREAM
Manufacturer: Shenzhen Ishan Technology Co., Ltd
Category: homeopathic | Type: HUMAN OTC DRUG LABEL
Date: 20260213

ACTIVE INGREDIENTS: OATMEAL 1 g/100 g
INACTIVE INGREDIENTS: CNIDIUM MONNIERI FRUIT 3 g/100 g; MAGNOLIA SIEBOLDII ROOT 3 g/100 g; BASSIA SCOPARIA FRUIT 3 g/100 g; MENTHOL 3 g/100 g; DICTAMNUS DASYCARPUS ROOT 3 g/100 g; STELLERA CHAMAEJASME WHOLE 3 g/100 g; SOPHORA FLAVESCENS ROOT 3 g/100 g

Active ingredients

Clotrimazole----1%----Antifungal

Inactive ingredients

Purify water, dictamnus dasycarpus root, cnidium monnieri fruit, menthol, magnolia sieboldii root, stellera chamaejasme whole, sophora flavescens root, bassia scoparia fruit.

Keep out of reach of children.

if swallowed, call poison control or seek medical help.

Ask a doctor if

use on children less than 2 years of age unless directed by a doctor

Stop use and ask a doctor if

Irritation occurs or there is no improvement of athlete's foot or ringworm within 4 weeks or jock intch with 2 weeks.

USES

Cures most athlete's foot (tinea pedis), jock itch (tinea cruris), ringworm (tinea corporis). Relieves itching, cracking, scaling, burning, irritation and discomforts which accompany these conditions.

Other information

Store at room temperature.

Directions

*Wash affected area and dry thoroughly
* Apply twice daily (morning and night) over the affected area , or as directed by a physician.
* Use daily for 4 weeks, pay special attention to the spaces between the toes; wear well-fitting ventilated shoes, and change shoes and socks at least once daily.
* Supervise children in the use of this product.
* This product is not proven to be effective on scalp or nails.
* Wash hands after each use.

Dosage & administration

Apply as needed

When using this product

Do not get into eyes.

Warning

For external use only.